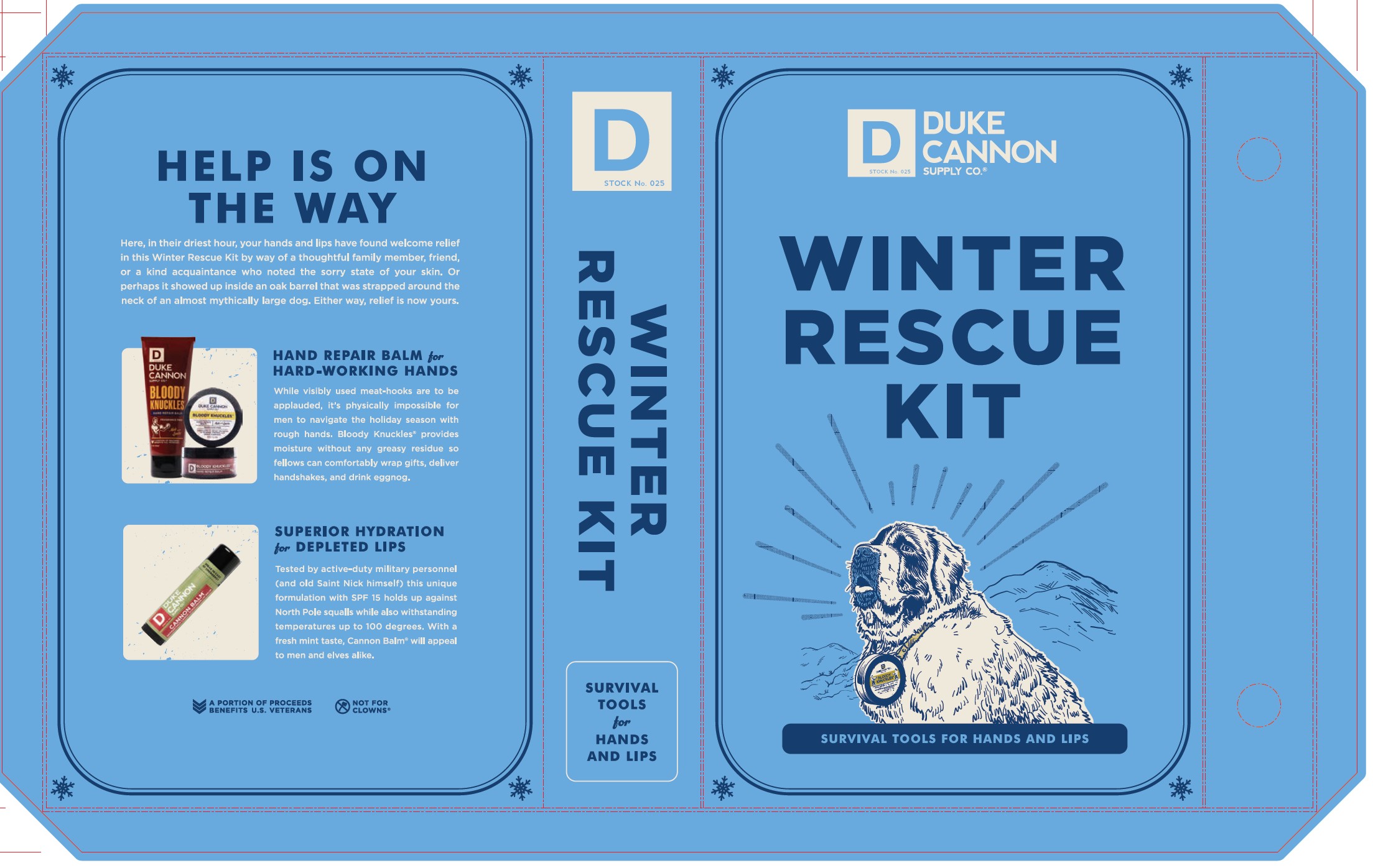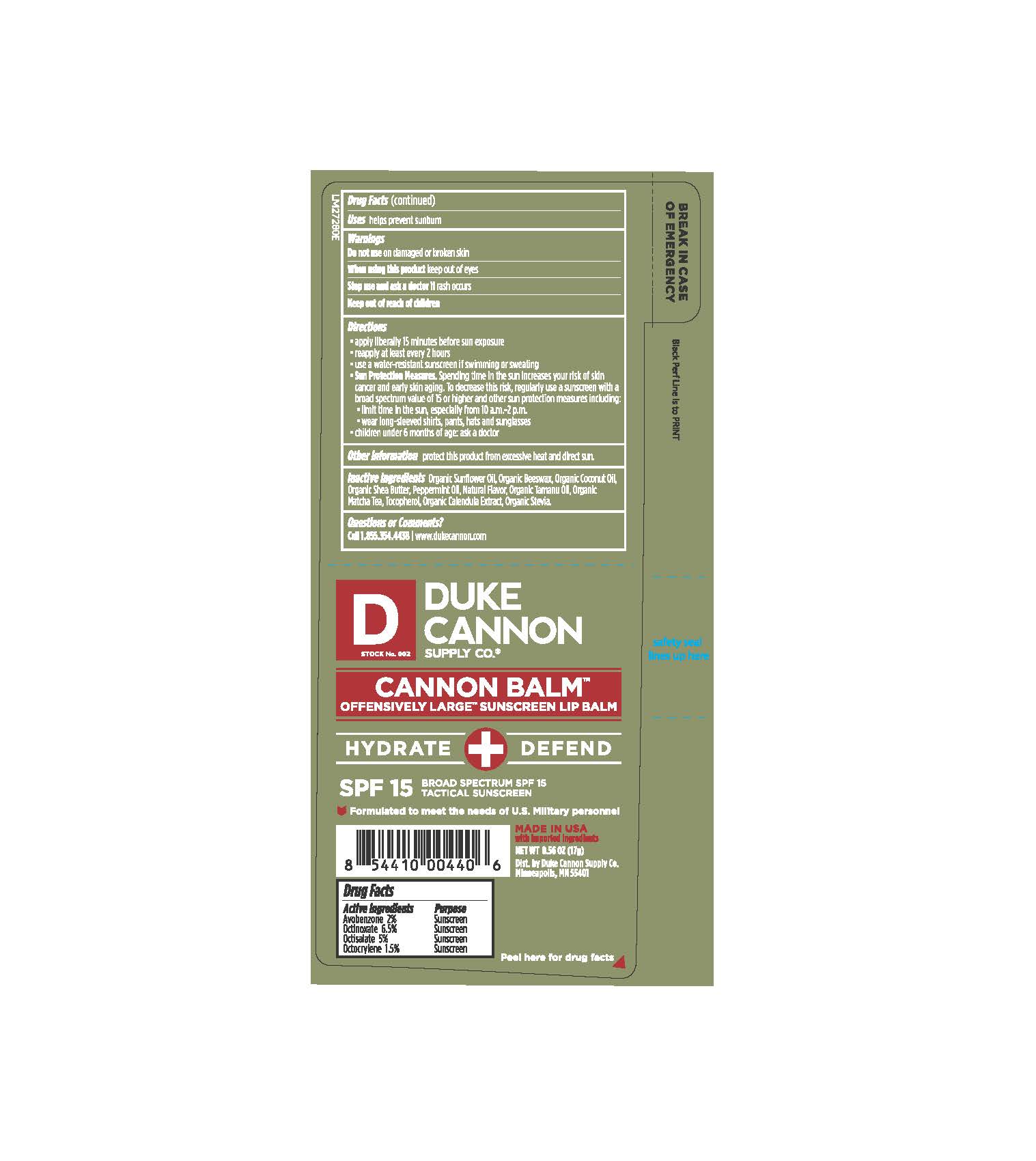 DRUG LABEL: Winter Rescue Kit
NDC: 71782-601 | Form: KIT | Route: TOPICAL
Manufacturer: DUKE CANNON SUPPLY CO.
Category: otc | Type: HUMAN OTC DRUG LABEL
Date: 20250429

ACTIVE INGREDIENTS: OCTOCRYLENE 0.255 g/17 g; AVOBENZONE 0.34 g/17 g; OCTINOXATE 1.105 g/17 g; OCTISALATE 0.85 g/17 g
INACTIVE INGREDIENTS: SUNFLOWER OIL; YELLOW WAX; COCONUT OIL; SHEA BUTTER; GREEN TEA LEAF; STEVIA REBAUDIUNA LEAF; CALENDULA OFFICINALIS FLOWER; PEPPERMINT OIL; TAMANU OIL; TOCOPHEROL

Winter Rescue Kit

Drug Facts

Active ingredients | Pupose
Avobenzone 2% | Sunscreen
Octinoxate 6.5% | Sunscreen
Octisalate 5% | Sunscreen
Octocylene 1.5% | Sunscreen

Uses

helps prevent sunburn

Warnings

Do not use

on damaged or broken skin

When using this product

keep out of eyes

Stop use and ask a doctor if

rash occurs

Keep out of reach of children

Directions

- apply liberally 15 minutes before sun exposure
- reapply at least every 2 house
- use a water-resistant sunscreen if swimming or sweating
- Sun protection meaures: spending time in the sun increases your risk of skin cancer and early skin aging. To decrease this risk, regularly use a sunscreen with a broad spectrum value of 15 or higher and other sun protection measures including:
  - limit time int he sun, especailly from 10 a.m.-2 p.m.
  - wear long-sleeved shirts, pants, hats, and sunglasses
  - children under 6 months of age: ask a doctor

Other Information

protect this product from excessive heat and direct sun.

Inactive ingredients

organic sunflower oil, organic beeswax, organic coconut oil, organic shea butter, peppermint oil, natural flavor, organic tamanu oil, organic matcha tea, tocopherol, organic calendula extract, organic stevia

Questions or comments?

call 1.855.354.4438 www.dukecannon.com

Tube Package

DUKE

CANNON

SUPPLY CO.

CANNON BALM

OFFENSIVELY LARGE SUNSCREEN LIP BALM

HYDRATE+DEFEND

SPF 15 BROAD SPECTRUM SPF 15

TACTICAL SUNSCREEN

Formulated to meet the needs of U.S. Military personnel

MADE IN USA

with imported ingredients.

Net Wt 0.56 oz (17g)

Dist. by Duke Cannon Supply Co.

Minneapolis, MN 55401

Peel here for drug facts

PACKAGE LABEL

DUKE CANNON SUPPLY CO.

Winter Rescue Kit

Survival Tools for Hands and Lips